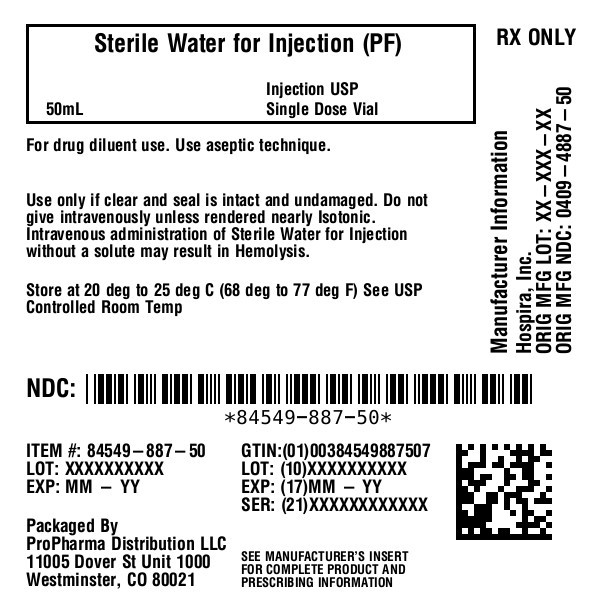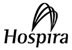 DRUG LABEL: Sterile Water
NDC: 84549-887 | Form: INJECTION
Manufacturer: ProPharma Distribution
Category: prescription | Type: HUMAN PRESCRIPTION DRUG LABEL
Date: 20251218

ACTIVE INGREDIENTS: WATER 1 mL/1 mL

Sterile Water Rx only
for Injection, USP

Glass Vial
Plastic Vial

DESCRIPTION

This preparation is designed solely for parenteral use only after addition of drugs that require dilution or must be dissolved in an aqueous vehicle prior to injection.

Sterile Water for Injection, USP is a sterile, nonpyrogenic preparation of water for injection which contains no bacteriostat, antimicrobial agent or added buffer and is supplied only in single-dose containers to dilute or dissolve drugs for injection. For I.V. injection, add sufficient solute to make an approximately isotonic solution.

Water for Injection, USP is chemically designated H2O.

The glass vial is Type I or II borosilicate glass and meets the requirements of the powdered glass test according to the USP standards.

The semi-rigid vial is fabricated from a specially formulated polyolefin. It is a copolymer of ethylene and propylene. The safety of the plastic has been confirmed by tests in animals according to USP biological standards for plastic containers. The container requires no vapor barrier to maintain the proper labeled volume.

CLINICAL PHARMACOLOGY

Water is an essential constituent of all body tissues and accounts for approximately 70% of total body weight. Average normal adult daily requirement ranges from two to three liters (1.0 to 1.5 liters each for insensible water loss by perspiration and urine production).

Water balance is maintained by various regulatory mechanisms. Water for distribution depends primarily on the concentration of electrolytes in the body compartments and sodium (Na^+) plays a major role in maintaining physiologic equilibrium.

The small volume of fluid provided by Sterile Water for Injection, USP when used only as a pharmaceutic aid for diluting or dissolving drugs for parenteral injection, is unlikely to exert a significant effect on fluid balance except possibly in neonates or very small infants.

INDICATIONS AND USAGE

This parenteral preparation is indicated only for diluting or dissolving drugs for intravenous, intramuscular or subcutaneous injection, according to instructions of the manufacturer of the drug to be administered.

CONTRAINDICATIONS

Sterile Water for Injection, USP must be made approximately isotonic prior to use.

WARNINGS

Intravenous administration of Sterile Water for Injection without a solute may result in hemolysis.

PRECAUTIONS

Do not use for intravenous injection unless the osmolar concentration of additives results in an approximate isotonic admixture.

Consult the manufacturer's instructions for choice of vehicle, appropriate dilution or volume for dissolving the drugs to be injected, including the route and rate of injection.

Inspect reconstituted (diluted or dissolved) drugs for clarity (if soluble) and freedom from unexpected precipitation or discoloration prior to administration.

Pregnancy:Animal reproduction studies have not been conducted with Sterile Water for Injection. It is also not known whether sterile water containing additives can cause fetal harm when administered to a pregnant woman or can affect reproduction capacity. Sterile Water for Injection with additives should be given to a pregnant woman only if clearly needed.

Pediatric Use

Safety and effectiveness have been established in pediatric patients. However, in neonates or very small infants the volume of fluid may affect fluid and electrolyte balance.

Drug Interactions

Some drugs for injection may be incompatible in a given vehicle, or when combined in the same vehicle or in a vehicle containing benzyl alcohol. Consult with pharmacist, if available.

Use aseptic technique for single or multiple entry and withdrawal from all containers.

When diluting or dissolving drugs, mix thoroughly and use promptly.

Do not store reconstituted solutions of drugs for injection unless otherwise directed by the manufacturer of the solute.

Do not use unless the solution is clear and seal intact. Do not reuse single-dose containers. Discard unused portion.

ADVERSE REACTIONS

Reactions which may occur because of this solution, added drugs or the technique of reconstitution or administration include febrile response, local tenderness, abscess, tissue necrosis or infection at the site of injection, venous thrombosis or phlebitis extending from the site of injection and extravasation.

If an adverse reaction does occur, discontinue the infusion, evaluate the patient, institute appropriate countermeasures, and if possible, retrieve and save the remainder of the unused vehicle for examination.

OVERDOSAGE

Use only as a diluent or solvent. This parenteral preparation is unlikely to pose a threat of fluid overload except possibly in neonates or very small infants. In the event these should occur, re-evaluate the patient and institute appropriate corrective measures. See WARNINGS, PRECAUTIONSand ADVERSE REACTIONS.

DOSAGE AND ADMINISTRATION

The volume of the preparation to be used for diluting or dissolving any drug for injection is dependent on the vehicle concentration, dose and route of administration as recommended by the manufacturer.

This parenteral should be inspected visually for particulate matter and discoloration prior to administration, whenever solution and container permit.

HOW SUPPLIED

Sterile Water for Injection, USP is supplied in the following:

NDC 84549-887-50

Single-dose Plastic Fliptop Vial

50 mL

Store at 20 to 25°C (68 to 77°F). [See USP Controlled Room Temperature.]